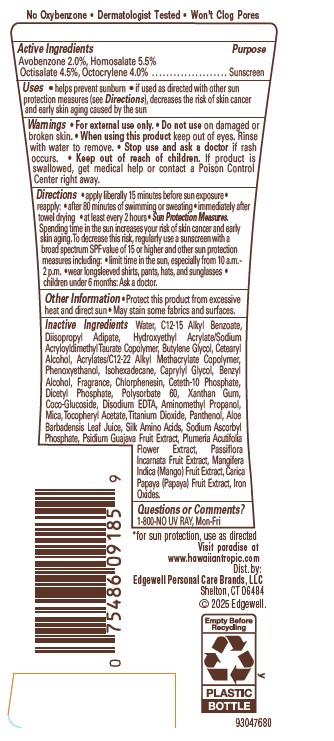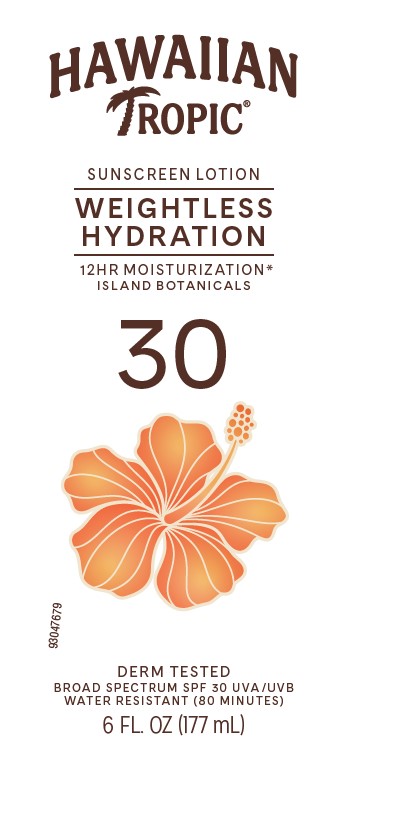 DRUG LABEL: Hawaiian Tropic Silk Hydration Sunscreen Broad Spectrum SPF 30
NDC: 63354-551 | Form: LOTION
Manufacturer: Edgewell Personal Care Brands, LLC
Category: otc | Type: HUMAN OTC DRUG LABEL
Date: 20260106

ACTIVE INGREDIENTS: OCTISALATE 4.5 g/100 g; AVOBENZONE 2 g/100 g; HOMOSALATE 5.5 g/100 g; OCTOCRYLENE 4 g/100 g
INACTIVE INGREDIENTS: DIHEXADECYL PHOSPHATE; SODIUM ASCORBYL PHOSPHATE; HYDROXYETHYL ACRYLATE/SODIUM ACRYLOYLDIMETHYL TAURATE COPOLYMER (45000 MPA.S AT 1%); BUTYLENE GLYCOL; POLYSORBATE 60; BENZYL ALCOHOL; ISOHEXADECANE; CAPRYLYL GLYCOL; CHLORPHENESIN; DIISOPROPYL ADIPATE; .ALPHA.-TOCOPHEROL ACETATE; PANTHENOL; PAPAYA; XANTHAN GUM; AMINOMETHYLPROPANOL; MICA; FERRIC OXIDE YELLOW; MANGO; GUAVA; CETETH-10 PHOSPHATE; EDETATE DISODIUM ANHYDROUS; COCO GLUCOSIDE; CETOSTEARYL ALCOHOL; PHENOXYETHANOL; PASSIFLORA INCARNATA FRUIT; TITANIUM DIOXIDE; ALOE VERA LEAF; AMINO ACIDS, SILK; PLUMERIA RUBRA FLOWER; ALKYL (C12-15) BENZOATE; WATER

Active Ingredients

Avobenzone 2.0%, Homosalate 5.5%, Octisalate 4.5%, Octocrylene 4.0%

Purpose

Sunscreen

Uses

• helps prevent sunburn • if used as directed with other sun protection measures (see Directions), decreases the risk of skin cancer and early skin aging caused by the sun

Warnings

For external use only.

May stain some fabrics.

Do not use

on damaged or broken skin

When using this product

keep out of eyes. Rinse with water to remove.

Stop use and ask a doctor

if rash occurs

Keep out of reach of children

If product is swallowed, get medical help or contact a Poison Control Center right away.

Directions

• apply liberally 15 minutes before sun exposure • reapply: • after 80 minutes of swimming or sweating • immediately after towel drying • at least every 2 hours • Sun Protection Measures. Spending time in the sun increases your risk of skin cancer and early skin aging. To decrease this risk, regularly use a sunscreen with a broad spectrum SPF value of 15 or higher and other sun protection measures including: • limit time in the sun, especially from 10 a.m. - 2 p.m. • wear long-sleeved shirts, pants, hats, and sunglasses • children under 6 months: Ask a doctor

Other information

protect this product from excessive heat and direct sun

Inactive ingredients

Water, C12-15 Alkyl Benzoate, Diisopropyl Adipate, Hydroxyethyl Acrylate/Sodium Acryloyldimethyl Taurate Copolymer, Butylene Glycol, Cetearyl Alcohol, Acrylates/C12-22Alkyl Methacrylate Copolymer, Phenoxyethanol, Isohexadecane, Caprylyl Glycol, Benzyl Alcohol, Fragrance, Chlorphenesin, Ceteth-10 Phosphate, Dicetyl Phosphate, Polysorbate 60, Xanthan Gum, Coco-Glucoside, Disodium EDTA, Aminomethyl Propanol, Mica, Tocopheryl Acetate, Titanium Dioxide, Panthenol, Aloe Barbadensis Leaf Juice, Silk Amino Acids, Sodium Ascorbyl Phosphate, Psidium Guajava Fruit, Extract, Plumeria Acutifolia Flower Extract, Passiflora Incarnata Fruit Extract, Mangifera Indica (Mango) Fruit Extract, Carica Papaya (Papaya) Fruit Extract, Iron Oxides

Questions or Comments?

Call 1-800-NO UV RAY, Mon-Fri

Primary Display Panel

HAWAIIAN

TROPIC

SUNSCREEN LOTION

WEIGHTLESS

HYDRATION

12 HR MOISTURIZATION*

ISLAND BOTANICALS

30

DERM TESTED

BROAD SPECTRUM SPF 30 UVA/UVB

WATER RESISTANT (80 MINUTES)

6 FL. OZ. (177mL)